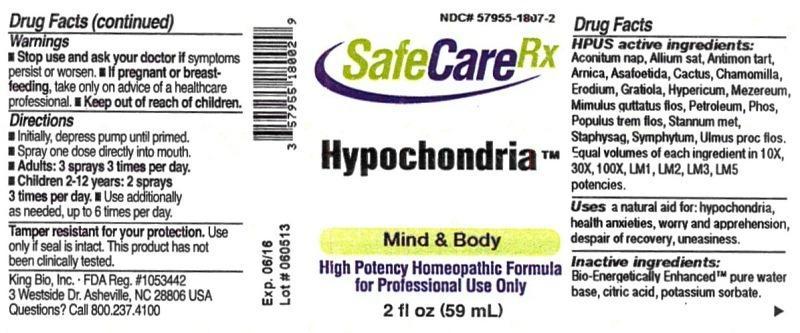 DRUG LABEL: Hypochondria
NDC: 57955-1807 | Form: LIQUID
Manufacturer: King Bio Inc.
Category: homeopathic | Type: HUMAN OTC DRUG LABEL
Date: 20150126

ACTIVE INGREDIENTS: ACONITUM NAPELLUS 10 [hp_X]/59 mL; GARLIC 10 [hp_X]/59 mL; ANTIMONY POTASSIUM TARTRATE 10 [hp_X]/59 mL; ARNICA MONTANA 10 [hp_X]/59 mL; ASAFETIDA 10 [hp_X]/59 mL; SELENICEREUS GRANDIFLORUS STEM 10 [hp_X]/59 mL; MATRICARIA RECUTITA 10 [hp_X]/59 mL; ERODIUM CICUTARIUM 10 [hp_X]/59 mL; GRATIOLA OFFICINALIS 10 [hp_X]/59 mL; HYPERICUM PERFORATUM 10 [hp_X]/59 mL; DAPHNE MEZEREUM BARK 10 [hp_X]/59 mL; MIMULUS GUTTATUS FLOWERING TOP 10 [hp_X]/59 mL; KEROSENE 10 [hp_X]/59 mL; PHOSPHORUS 10 [hp_X]/59 mL; POPULUS TREMULA FLOWERING TOP 10 [hp_X]/59 mL; TIN 10 [hp_X]/59 mL; DELPHINIUM STAPHISAGRIA SEED 10 [hp_X]/59 mL; COMFREY ROOT 10 [hp_X]/59 mL; ULMUS PROCERA FLOWERING TWIG 10 [hp_X]/59 mL
INACTIVE INGREDIENTS: WATER; ANHYDROUS CITRIC ACID; POTASSIUM SORBATE

Hypochochondria™

Drug Facts

____________________________________________________________________________________________________________

HPUS active ingredients: Aconitum napellus, Allium sativum, Antimonium tartaricum, Arnica montana, Asafoetida, Cactus grandiflorus, Chamomilla, Erodium, Gratiola officinalis, Hypericum perforatum, Mezereum, Mimulus guttatus, flos, Petroleum, Phosphorus, Populus tremula, flos, Stannum metallicum, Staphysagria, Symphytum officinale, Ulmus procera, flos. Equal volumes of each ingredient in 10X, 30X, 100X, LM1, LM2, LM3, LM5 potencies.

INDICATIONS AND USAGE

Uses a natural aid for:

- hypochondria
- health anxieties
- worry and apprehension
- despair of recovery
- uneasiness.

INACTIVE INGREDIENT

Inactive ingredients: Bio-Energetically Enhanced pure water base, citric acid, potassium sorbate.

Warnings

- Stop use and ask your doctor if symptoms persist or worsen.
- If pregnant or breast-feeding, take only on advice of a healthcare professional.

- Keep out of reach of children.

Directions:

- Initially, depress pump until primed.
- Spray one dose directly into mouth.
- Adults: 3 sprays 3 times per day.
- Children 2-12 years: 2 sprays 3 times per day.
- Use additionally as needed, up to 6 times per day.

OTHER SAFETY INFORMATION

Tamper resistant for your protection. Use only if safety seal is intact.

PURPOSE

Uses a natural aid for: hypochondria, health anxieties, worry and apprehension, despair of recovery, uneasiness.